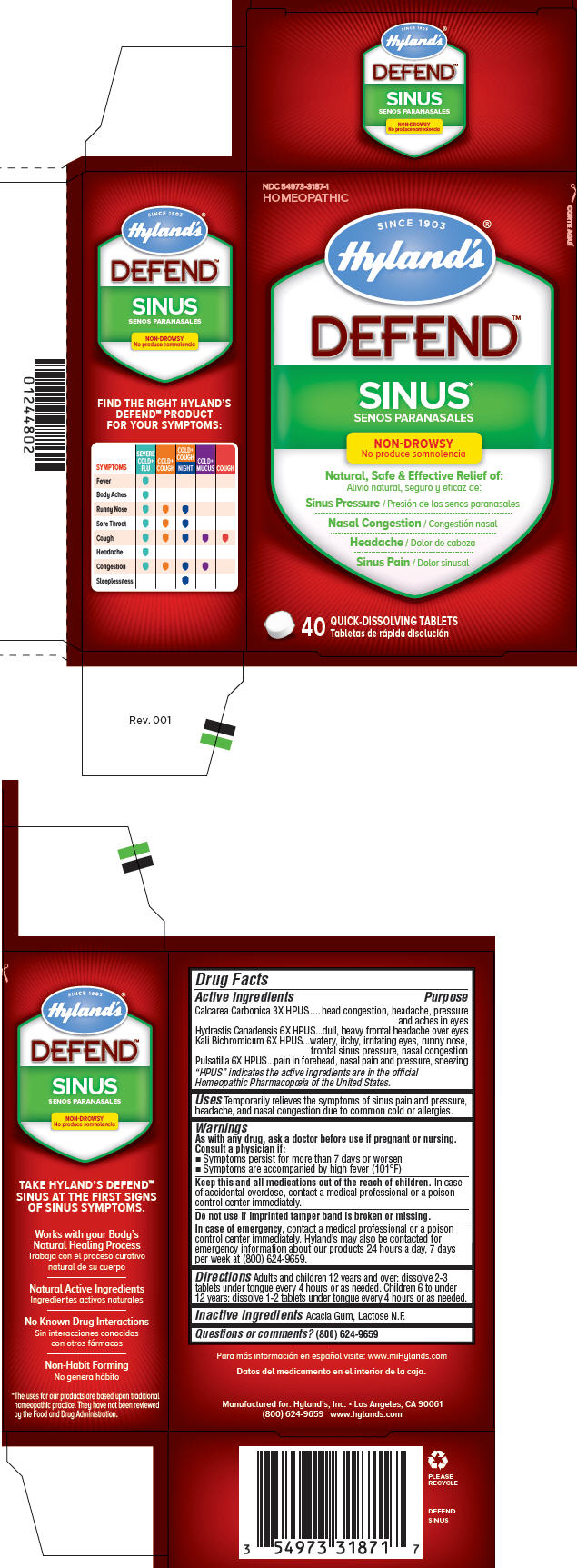 DRUG LABEL: DEFEND Sinus
NDC: 54973-3187 | Form: TABLET, SOLUBLE
Manufacturer: Hyland's Inc.
Category: homeopathic | Type: HUMAN OTC DRUG LABEL
Date: 20221212

ACTIVE INGREDIENTS: OYSTER SHELL CALCIUM CARBONATE, CRUDE 3 [hp_X]/1 1; GOLDENSEAL 6 [hp_X]/1 1; POTASSIUM DICHROMATE 6 [hp_X]/1 1; PULSATILLA VULGARIS 6 [hp_X]/1 1
INACTIVE INGREDIENTS: ACACIA; LACTOSE

Defend™ Sinus

Drug Facts

ACTIVE INGREDIENT

Active ingredients | Purpose
Calcarea Carbonica 3X HPUS | head congestion, headache, pressure and aches in eyes
Hydrastis Canadensis 6X HPUS | dull, heavy frontal headache over eyes
Kali Bichromicum 6X HPUS | watery, itchy, irritating eyes, runny nose, frontal sinus pressure, nasal congestion
Pulsatilla 6X HPUS | pain in forehead, nasal pain and pressure, sneezing
"HPUS" indicates the active ingredients are in the official Homeopathic Pharmacopœia of the United States.

Uses

Temporarily relieves the symptoms of sinus pain and pressure, headache, and nasal congestion due to common cold or allergies.

Warnings

ASK DOCTOR

As with any drug, ask a doctor before use if pregnant or nursing. Consult a physician if:

- Symptoms persist for more than 7 days or worsen
- Symptoms are accompanied by high fever (101°F)

KEEP OUT OF REACH OF CHILDREN

Keep this and all medications out of the reach of children. In case of accidental overdose, contact a medical professional or a poison control center immediately.

Do not use if imprinted tamper band is broken or missing.

ASK DOCTOR/PHARMACIST

In case of emergency, contact a medical professional or a poison control center immediately. Hyland's may also be contacted for emergency information about our products 24 hours a day, 7 days per week at (800) 624-9659.

Directions

Adults and children 12 years and over: dissolve 2-3 tablets under tongue every 4 hours or as needed. Children 6 to under 12 years: dissolve 1-2 tablets under tongue every 4 hours or as needed.

Inactive ingredients

Acacia Gum, Lactose N.F.

Questions or comments?

(800) 624-9659

PRINCIPAL DISPLAY PANEL - 40 Tablet Bottle Carton

NDC 54973-3187-1
HOMEOPATHIC

SINCE 1903
Hyland's

DEFEND™

SINUS*

NON-DROWSY

Natural, Safe & Effective Relief of:

Sinus Pressure

Nasal Congestion

Headache

Sinus Pain

40
QUICK-DISSOLVING TABLETS